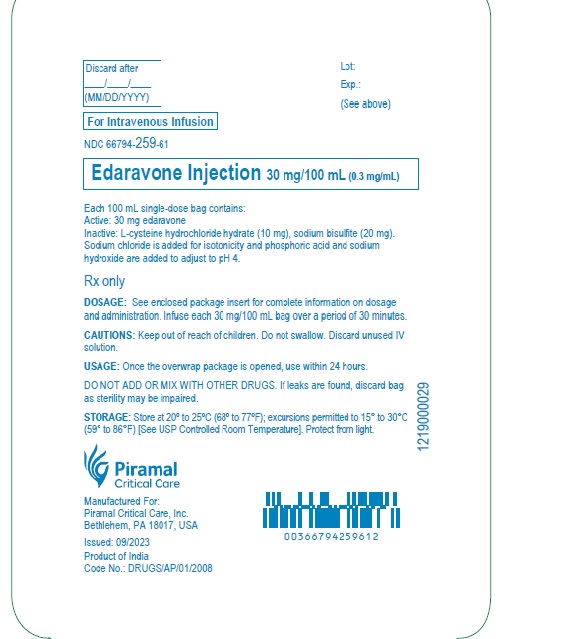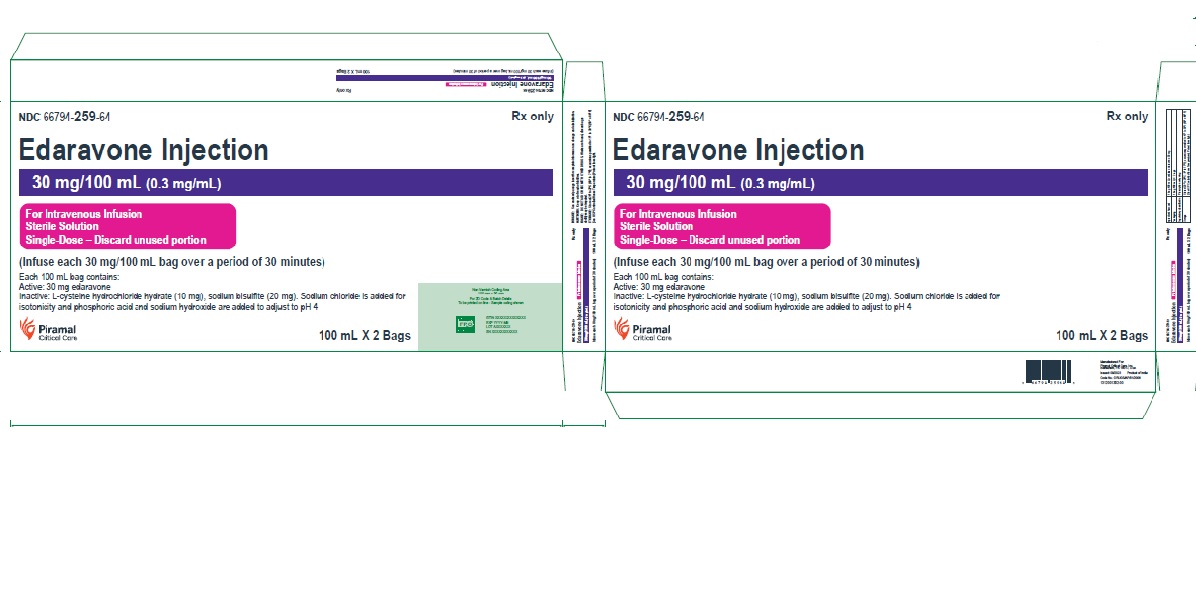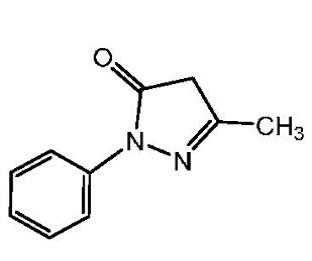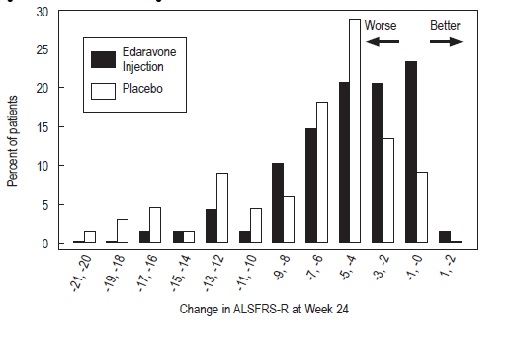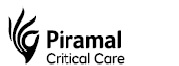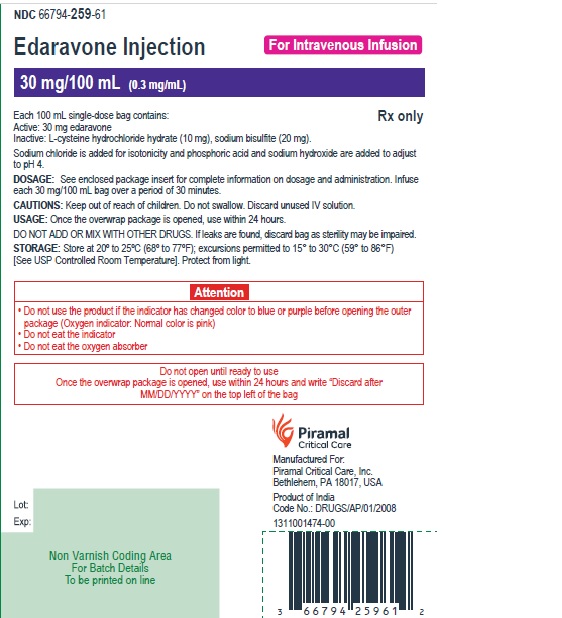 DRUG LABEL: Edaravone
NDC: 66794-259 | Form: INJECTION, SOLUTION
Manufacturer: Piramal Critical Care Inc.
Category: prescription | Type: HUMAN PRESCRIPTION DRUG LABEL
Date: 20251007

ACTIVE INGREDIENTS: EDARAVONE 30 mg/100 mL
INACTIVE INGREDIENTS: CYSTEINE HYDROCHLORIDE; SODIUM CHLORIDE; SODIUM HYDROXIDE; PHOSPHORIC ACID; WATER; SODIUM BISULFITE

HIGHLIGHTS OF PRESCRIBING INFORMATION

These highlights do not include all the information needed to use EDARAVONE INJECTION safely and effectively. See full prescribing information for EDARAVONE INJECTION.
EDARAVONE injection, for intravenous use
Initial U.S. Approval: 2017

1 INDICATIONS AND USAGE

Edaravone injection is indicated for the treatment of amyotrophic lateral sclerosis (ALS) (1)

2 DOSAGE AND ADMINISTRATION

- Edaravone Injection: The recommended dosage is 60 mg administered as an intravenous infusion over 60 minutes as follows (2.1)
- Initial treatment cycle: daily dosing for 14 days followed by a 14 day drug-free period (2.1)
- Subsequent treatment cycles: daily dosing for 10 days out of 14 day periods, followed by 14-day drug-free periods (2.1)

3 DOSAGE FORMS AND STRENGTHS

Injection: 30 mg/100 mL in a single-dose polypropylene bag (3)

4 CONTRAINDICATIONS

Patients with a history of hypersensitivity to edaravone or any of the inactive ingredients in edaravone injection (4)

5 WARNINGS AND PRECAUTIONS

- Hypersensitivity Reactions: Advise patients to seek immediate medical care (5.1)
- Sulfite Allergic Reactions: Edaravone injection contains sodium bisulfite, which may cause allergic type reactions including anaphylactic symptoms and asthmatic episodes in susceptible people (5.2)

6 ADVERSE REACTIONS

Most common adverse reactions (at least 10% of patients treated with edaravone injection and greater than placebo) are contusion, gait disturbance, and headache (6.1)

To report SUSPECTED ADVERSE REACTIONS, contact Piramal Crtical Care, Inc. at 1-800-414-1901 or FDA at 1-800-FDA-1088 or www.fda.gov/medwatch.

8 USE IN SPECIFIC POPULATIONS

• Pregnancy: Based on animal data, may cause fetal harm. (8.1)

See 17 for PATIENT COUNSELING INFORMATION and FDA-approved patient labeling.

Revised: 09/2023

FULL PRESCRIBING INFORMATION

1 INDICATIONS AND USAGE

Edaravone injection is indicated for the treatment of amyotrophic lateral sclerosis (ALS).

2 DOSAGE AND ADMINISTRATION

2.1 Dosage Information

- The recommended dosage of edaravone injection: an intravenous infusion of 60 mg administered over a 60-minute period.

Administer Edaravone injection according to the following schedule:

- An initial treatment cycle with daily dosing for 14 days, followed by a 14-day drug-free period
- Subsequent treatment cycles with daily dosing for 10 days out of 14-day periods, followed by 14-day drug-free periods.

2.2 Preparation and Administration Information for Edaravone Injection

Edaravone injection is for intravenous infusion only.

Preparation

Do not use if the oxygen indicator has turned blue or purple before opening the package .Once the overwrap package is opened, use within 24 hours [see How Supplied/Storage and Handling (16.1, 16.2)].

Parenteral drug products should be inspected visually for particulate matter and discoloration prior to administration, whenever solution and container permit. Discard unused portion.

Administration

Administer a 60 mg dose of edaravone injection as two consecutive 30 mg intravenous infusion bag over a total of 60 minutes (infusion rate approximately 1 mg per minute [3.33 mL per minute]).

Promptly discontinue the infusion upon the first observation of any signs or symptoms consistent with a hypersensitivity reaction [see Warnings and Precautions (5.1, 5.2)] .

Other medications should not be injected into the infusion bag or mixed with edaravone injection.

2.4 Switching from Edaravone Injection to RADICAVA ORS

Patients treated with 60 mg of edaravone injection intravenous infusion may be switched to 105 mg (5 mL) Radicava ORS using the same dosing frequency.

3 DOSAGE FORMS AND STRENGTHS

Edaravone injection is supplied for intravenous infusion in a single-dose polypropylene bag containing 30 mg of edaravone in 100 mL of clear, colorless aqueous solution.

4 CONTRAINDICATIONS

Edaravone injection is contraindicated in patients with a history of hypersensitivity to edaravone or any of the inactive ingredients in this product. Hypersensitivity reactions and anaphylactic reactions have occurred [see Warnings and Precautions (5.1, 5.2)].

5 WARNINGS AND PRECAUTIONS

5.1 Hypersensitivity Reactions

Hypersensitivity reactions (redness, wheals, and erythema multiforme) and cases of anaphylaxis (urticaria, decreased blood pressure, and dyspnea) have been reported in spontaneous postmarketing reports with edaravone injection.

Patients should be monitored carefully for hypersensitivity reactions. If hypersensitivity reactions occur, discontinue edaravone injection, treat per standard of care, and monitor until the condition resolves [see Contraindications (4)] .

5.2 Sulfite Allergic Reactions

Edaravone injection contains sodium bisulfite, a sulfite that may cause allergic type reactions, including anaphylactic symptoms and life-threatening or less severe asthmatic episodes in susceptible people. The overall prevalence of sulfite sensitivity in the general population is unknown. Sulfite sensitivity occurs more frequently in asthmatic than non-asthmatic people.

6 ADVERSE REACTIONS

The following serious adverse reactions are described elsewhere in the labeling:
• Hypersensitivity Reactions [see Warnings and Precautions (5.1)]
• Sulfite Allergic Reactions [see Warnings and Precautions (5.2)]

6.1 Clinical Trials Experience

Because clinical trials are conducted under widely varying conditions, adverse reaction rates observed in the clinical trials of a drug cannot be directly compared to rates in the clinical trials of another drug and may not reflect the rates observed in practice.

In randomized, placebo-controlled trials, 184 patients with ALS were administered edaravone injection 60 mg in treatment cycles for 6 months. The population consisted of Japanese patients who had a median age of 60 years (range 29 to 75) and were 59% male. Most (93%) of these patients were living independently at the time of screening.

Most Common Adverse Reactions Observed During Clinical Studies
Table 2 lists the adverse reactions that occurred in ≥ 2% of patients in the edaravone injection-treated group and that occurred at least 2% more frequently than in the placebo-treated group in randomized placebo-controlled ALS trials. The most common adverse reactions that occurred in ≥ 10% of edaravone injection-treated patients were contusion, gait disturbance, and headache.
Table 2: Adverse Reactions from Pooled Placebo-Controlled Trialsathat Occurred in ≥ 2% of Edaravone Injection-Treated Patients and ≥ 2% More Frequently than in Placebo Patients

Adverse Reaction | Edaravone Injection (N=184) % | Placebo (N=184) %
Contusion | 15 | 9
Gait disturbance | 13 | 9
Headache | 10 | 6
Dermatitis | 8 | 5
Eczema | 7 | 4
Respiratory failure, respiratory disorder, hypoxia | 6 | 4
Glycosuria | 4 | 2
Tinea infection | 4 | 2

a Pooled placebo-controlled studies include two additional studies with 231 additional patients, all using the same treatment regimen [see Clinical Studies (14)].

6.2 Postmarketing Experience

The following adverse reactions have been identified during postapproval use of edaravone injection. Because these reactions are reported voluntarily from a population of uncertain size, it is not always possible to reliably estimate their frequency or establish a causal relationship to drug exposure.

Skin and subcutaneous tissue disorders: Hypersensitivity reactions and anaphylaxis. [see Warnings and Precautions (5.1, 5.2)].

8 USE IN SPECIFIC POPULATIONS

8.1 Pregnancy

Risk Summary
There are no adequate data on the developmental risk associated with the use of edaravone injection in pregnant women. In animal studies, administration of edaravone to pregnant rats and rabbits resulted in adverse developmental effects (increased mortality, decreased growth, delayed sexual development, and altered behavior) at clinically relevant doses. Most of these effects occurred at doses that were also associated with maternal toxicity (see Animal Data).
In the U.S. general population, the estimated background risk of major birth defects and miscarriage in clinically recognized pregnancies is 2 to 4% and 15 to 20%, respectively. The background risk for major birth defects and miscarriage in patients with ALS is unknown.
Data
Animal Data

In rats, intravenous administration of edaravone (0, 3, 30, or 300 mg/kg/day) throughout the period of organogenesis resulted in reduced fetal weight at all doses. In dams allowed to deliver naturally, offspring weight was reduced at the highest dose tested. Maternal toxicity was also observed at the highest dose tested. There were no adverse effects on reproductive function in the offspring. A no-effect dose for embryofetal developmental toxicity was not identified; the low dose is less than the recommended human dose of 60 mg for edaravone injection, on a body surface area (mg/m^2) basis.

In rabbits, intravenous administration of edaravone (0, 3, 20, or 100 mg/kg/day) throughout the period of organogenesis resulted in embryofetal death at the highest dose tested, which was associated with maternal toxicity. The higher no-effect dose for embryofetal developmental toxicity is approximately 6 times the recommended human dose (RHD) for edaravone injection on a body surface area (mg/m^2) basis.
The effects on offspring of edaravone (0, 3, 20, or 200 mg/kg/day), administered by intravenous injection to rats from GD 17 throughout lactation, were assessed in two studies. In the first study, offspring mortality was observed at the high dose and increased activity was observed at the mid and high doses. In the second study, there was an increase in stillbirths, offspring mortality, and delayed physical development (vaginal opening) at the highest dose tested. Reproduction function in offspring was not affected in either study. Maternal toxicity was evident in both studies at all but the lowest dose tested. The no-effect dose for developmental toxicity (3 mg/kg/day) is less than the RHD on a mg/m^2basis.

8.2 Lactation

Risk Summary
There are no data on the presence of edaravone in human milk, the effects on the breastfed infant, or the effects of the drug on milk production. Edaravone and its metabolites are excreted in the milk of lactating rats. The developmental and health benefits of breastfeeding should be considered along with the mother’s clinical need for edaravone injection and any potential adverse effects on the breastfed infant from edaravone injection or from the underlying maternal condition.

8.4 Pediatric Use

Safety and effectiveness of edaravone injection in pediatric patients have not been established.

8.5 Geriatric Use

Of the 184 patients with ALS who received edaravone injection in 3 placebo-controlled clinical trials, a total of 53 patients were 65 years of age and older, including 2 patients 75 years of age and older. No overall differences in safety or effectiveness were observed between these patients and younger patients, but greater sensitivity of some older individuals cannot be ruled out.

11 DESCRIPTION

The active ingredient in edaravone injection is edaravone, which is a member of the substituted 2-pyrazolin-5-one class. The chemical name of edaravone is [3-methyl-1-phenyl-2-pyrazolin-5-one]. The molecular formula is C10H10N2O and the molecular weight is 174.20.

The chemical structure is:

Edaravone is a white crystalline powder with a melting point of 129.7°C. It is freely soluble in acetic acid, methanol, or ethanol and slightly soluble in water or diethyl ether.
Edaravone injection is a clear, colorless liquid provided as a sterile solution.
Edaravone injection is supplied for intravenous infusion in a polypropylene bag containing 30 mg edaravone in 100 mL isotonic, sterile, aqueous solution, which is further overwrapped with clear pouch. The overwrapped package also contains an oxygen absorber and oxygen indicator to minimize oxidation. Clear pouch is further overwrapped in PET pouch. Each bag contains the following inactive ingredients: L-cysteine hydrochloride hydrate (10 mg), sodium bisulfite (20 mg). Sodium chloride is added for isotonicity and phosphoric acid and sodium hydroxide are added to adjust to pH 4.

12 CLINICAL PHARMACOLOGY

12.1 Mechanism of Action

The mechanism by which edaravone injection exert its therapeutic effect in patients with ALS is unknown.

12.2 Pharmacodynamics

Cardiac Electrophysiology

At exposures at least 5 times higher than that of the recommended doses of Edaravone injection, edaravone does not prolong the QT interval to any clinically relevant extent.

12.3 Pharmacokinetics

Edaravone injection is administered by IV infusion. The maximum plasma concentration (Cmax) of edaravone was reached by the end of infusion. There was a trend of more than dose-proportional increase in area under the concentration-time curve (AUC) and Cmax of edaravone. With multiple-dose administration, edaravone does not accumulate in plasma.

Distribution

Edaravone is bound to human serum proteins (92%), mainly to albumin, with no concentration dependence in the range of 0.1 to 50 micromol/L. Edaravone has a mean volume of distribution after intravenous administration of 63.1 L.

Elimination

The mean terminal elimination half-life of edaravone is approximately 4.5 to 9 hours. The half-lives of its metabolites are 3 to 6 hours. Following intravenous administration, the total clearance of edaravone is estimated to be 35.9 L/h.

Metabolism

Edaravone is metabolized to a sulfate conjugate and a glucuronide conjugate, which are not pharmacologically active. The glucuronide conjugation of edaravone involves multiple uridine diphosphate glucuronosyltransferase (UGT) isoforms (UGT1A1, UGT1A6, UGT1A7, UGT1A8, UGT1A9, UGT1A10, UGT2B7, and UGT2B17). In human plasma, edaravone is mainly detected as the sulfate conjugate, which is presumed to be formed by sulfotransferases.

Excretion

In Japanese and Caucasian healthy volunteer studies, edaravone was excreted mainly in the urine as its glucuronide conjugate (60-80% of the dose up to 48 hours). Approximately 6-8% of the dose was recovered in the urine as the sulfate conjugate, and < 1% of the dose was recovered in the urine as the unchanged drug. In vitro studies suggest that the sulfate conjugate of edaravone is hydrolyzed back to edaravone, which is then converted to the glucuronide conjugate in the kidney before excretion into the urine.

Specific Populations

Geriatric Patients

No age effect on edaravone pharmacokinetics has been found [see Use in Specific Populations (8.5)].

Patients with Renal Impairment

Following single IV infusion of 30 mg edaravone (half the recommended dosage of edaravone injection) over 60 minutes, mean Cmaxand AUC0-∞of unchanged edaravone were 1.15 and 1.20-fold greater in the subjects with mild renal impairment (eGFR 60 to 89 mL/min/1.73m^2), and were 1.25 and 1.29-fold greater in the subjects with moderate renal impairment (eGFR 30 to 59 mL/min/1.73m^2) when compared to subjects with normal renal function, respectively. These changes in exposures are not considered to be clinically significant and therefore no dosage adjustments are necessary in patients with mild to moderate renal impairment. The effects of severe renal impairment on the pharmacokinetics of edaravone have not been studied.

Patients with Hepatic Impairment

Following single IV infusion of 30 mg edaravone (half of the recommended dose of edaravone injection) over 60 minutes, mean Cmaxand AUC0-∞of unchanged edaravone were 1.20 and 1.07-fold greater in the subjects with mild hepatic impairment (Child-Pugh score 5 or 6), were 1.24 and 1.14-fold greater in the subjects with moderate hepatic impairment (Child-Pugh score 7 to 9), and were 1.20 and 1.19-fold greater in the subjects with severe hepatic impairment (Child-Pugh score 10 to 14) when compared to subjects with normal hepatic function, respectively. These changes in exposures are not considered to be clinically significant and therefore no dosage adjustments are necessary in patients with hepatic impairment.

Male and Female Patients

No gender effect on edaravone pharmacokinetics has been found.

Racial or Ethnic Groups

There were no significant racial differences in Cmaxand AUC of edaravone between Japanese and Caucasian subjects.

Drug Interaction Studies

The pharmacokinetics of edaravone is not expected to be significantly affected by inhibitors of cytochrome P450 (CYP) enzymes, UGTs, or major transporters.

In vitrostudies demonstrated that, at the recommended dosage, edaravone and its metabolites are not expected to significantly inhibit CYP enzymes (CYP1A2, CYP2B6, CYP2C8, CYP2C9, CYP2C19, CYP2D6, and CYP3A), conjugating enzymes UGT1A1 and UGT2B7, or other transporters (P-gp, OATP1B1, OATP1B3, OAT1, OCT2, MATE1, and MATE2-K) in humans. Edaravone and its metabolites are not expected to induce CYP1A2, or CYP2B6, at the recommended dosage of edaravone.

In vitro data indicated that edaravone was not a substrate of OATP1B1 or OATP1B3.

13 NONCLINICAL TOXICOLOGY

13.1 Carcinogenesis, Mutagenesis, Impairment of Fertility

Carcinogenesis

Carcinogenicity studies of edaravone using the intravenous route have not been conducted.

Mutagenesis

Edaravone was negative in in vitro(bacterial reverse mutation and Chinese hamster lung chromosomal aberration) and in vivo(mouse micronucleus) assays.

Impairment of Fertility

Intravenous administration of edaravone (0, 3, 20, or 200 mg/kg) prior to and throughout mating in male and female rats and continuing in females to gestation day 7 had no effect on fertility; however, disruption of the estrus cycle and mating behavior was observed at the highest dose tested. No effects on reproductive function were observed at the lower doses, which are up to approximately 3 times the RHD for edaravone injection (60 mg) on a body surface area (mg/m^2) basis.

14 CLINICAL STUDIES

The efficacy of edaravone injection for the treatment of ALS was established in a 6-month, randomized, placebo-controlled, double-blind study conducted in Japanese patients with ALS who were living independently and met the following criteria at screening:
1. Functionality retained most activities of daily living (defined as scores of 2 points or better on each individual item of the ALS Functional Rating Scale – Revised [ALSFRS-R; described below])
2. Normal respiratory function (defined as percent-predicted forced vital capacity values of [%FVC] ≥ 80%)
3. Definite or Probable ALS based on El Escorial revised criteria
4. Disease duration of 2 years or less
The study enrolled 69 patients in the edaravone injection arm and 68 in the placebo arm. Baseline characteristics were similar between these groups, with over 90% of patients in each group being treated with riluzole.
Edaravone injection was administered as an intravenous infusion of 60 mg given over a 60 minute period according to the following schedule:
• An initial treatment cycle with daily dosing for 14 days, followed by a 14-day drug-free period (Cycle 1)
• Subsequent treatment cycles with daily dosing for 10 days out of 14-day periods, followed by 14-day drug-free periods (Cycles 2 to 6).
The primary efficacy endpoint was a comparison of the change between treatment arms in the ALSFRS-R total scores from baseline to Week 24. The ALSFRS-R scale consists of 12 questions that evaluate the fine motor, gross motor, bulbar, and respiratory function of patients with ALS (speech, salivation, swallowing, handwriting, cutting food, dressing/hygiene, turning in bed, walking, climbing stairs, dyspnea, orthopnea, and respiratory insufficiency). Each item is scored from 0 to 4, with higher scores representing greater functional ability. The decline in ALSFRS-R scores from baseline was significantly less in the edaravone injection-treated patients as compared to placebo (see Table 3). The distribution of change in ALSFRS-R scores from baseline to Week 24 by percent of patients is shown in Figure 1.

Table 3: Analysis of Change from Baseline to Week 24 in ALSFRS-R Scores

Treatment | Change from Baseline LS Mean ± SE (95% CI) | Treatment Difference (Edaravone Injection– placebo [95% CI]) | p-value
Edaravone injection | −5.01±0.64 | 2.49 (0.99, 3.98) | 0.0013
Placebo | −7.50±0.66

Figure 1: Distribution of Change from Baseline to Week 24 in ALSFRS-R Scores

16 HOW SUPPLIED/STORAGE AND HANDLING

16.1 How Supplied

Edaravone injection is supplied as a 30 mg/100 mL (0.3 mg/mL) clear, colorless, sterile solution for intravenous infusion in a single-dose polypropylene bags, each overwrapped with clear pouch secondary packaging containing an oxygen absorber and oxygen indicator, which should be pink to reflect appropriate oxygen levels and clear pouch is further overwrapped in PET pouch [see Dosage and Administration (2.2) and How Supplied/Storage and Handling (16.2)] . These are supplied in cartons as listed below.
NDC 66794-259-61 30 mg/100 mL (0.3 mg/mL) single-dose bag

NDC 66794-259-64 2 bags per carton

16.2 Storage and Handling

Store Edaravone Injection at 20º to 25ºC (68º to 77ºF); excursions permitted from 15° to 30°C (59° to 86°F) [See USP Controlled Room Temperature]. Protect from light. Store in overwrapped package to protect from oxygen degradation until time of use. The oxygen indicator will turn blue or purple if the oxygen has exceeded acceptable levels. Once the overwrap package is opened, use within 24 hours.

17 PATIENT COUNSELING INFORMATION

Advise the patients to read the FDA-approved patient labeling (Patient Information).

Hypersensitivity Reactions
Advise patients to seek immediate medical care if they experience signs or symptoms of a hypersensitivity reaction [see Warnings and Precautions (5.1)].
Sulfite Allergic Reactions
Advise patients about potential for sulfite sensitivity. Inform patients that edaravone injection contains sodium bisulfite, which may cause allergic type reactions including anaphylactic symptoms and life-threatening or less severe asthmatic episodes, and to seek immediate medical care if they experience these signs or symptoms [see Warnings and Precautions (5.2)].
Pregnancy and Breastfeeding
Advise patients to notify their healthcare provider if they become pregnant or intend to become pregnant during edaravone injection therapy [see Use in Specific Populations (8.1)].
Advise patients to notify their healthcare provider if they intend to breastfeed or are breastfeeding an infant [see Use in Specific Populations (8.2)].

Manufactured for:
Piramal Crtical Care, Inc.
Bethlehem, PA 18017, USA

Issued: 09/2023

PATIENT INFORMATION
Edaravone Injection (e-dar-a-vone)
for intravenous use

What is Edaravone Injection?
Edaravone injection is a prescription medicine used to treat people with amyotrophic lateral sclerosis (ALS). It is not known if edaravone injection is safe and effective in children.
Do not receive edaravone injection if you are allergic to edaravone or any of the ingredients in edaravone injection. See the end of this leaflet for a complete list of ingredients in edaravone injection.
Before you receive edaravone injection, tell your healthcare provider about all of your medical conditions, including if you:

- have asthma.
- are allergic to other medicines.
- are pregnant or plan to become pregnant. It is not known if edaravone injection will harm your unborn baby.
- are breastfeeding or plan to breastfeed. It is not known if edaravone passes into your breastmilk.
- You and your healthcare provider should decide if you will receive edaravone injection or breastfeed.

Tell your healthcare provider about all the medicines you take, including prescription and over-the-counter medicines, vitamins, and herbal supplements.
How will I receive edaravone injection?

- You will be prescribed edaravone injection by a healthcare provider and told how often you will receive edaravone injection.
- Edaravone Injection will be given by intravenous (IV) infusion into your vein.
- It takes about 1 hour to receive the full dose of edaravone injection.
- Your healthcare provider will monitor you closely during your treatment with edaravone injection.

What are the possible side effects of edaravone injection?
Edaravone injection may cause serious side effects including:
1. Hypersensitivity (allergic) reactions. Hypersensitivity reactions have happened in people receiving edaravone injection and can happen after your medicine has been given. Tell your healthcare provider right away or go to the nearest emergency room if you have any of the following symptoms:
• hives • swelling of the lips, tongue, face • fainting
• breathing problems • dizziness
• itching • wheezing

2. Sulfite allergic reactions. Edaravone injection contains sodium bisulfite, a sulfite that may cause a type of allergic reaction that can be serious and life-threatening. Sodium bisulfite can also cause less severe allergic reactions, for example, asthma episodes, in certain people. Sulfite sensitivity can happen more often in people who have asthma than in people who do not have asthma. Tell your healthcare provider right away or go to the nearest emergency room if you have any of the following symptoms:

• hives • swelling of the lips, tongue, face • wheezing
• trouble breathing or swallowing • dizziness • fainting
• itching • asthma attack (in people with asthma)

Your healthcare provider will monitor you during treatment to watch for signs and symptoms of all the serious side effects and allergic reactions.

The most common side effects of edaravone injection include bruising (contusion), problems walking (gait disturbance), and headache.

These are not all the possible side effects of edaravone injection. For more information, ask your healthcare provider or pharmacist.

Call your doctor for medical advice about side effects. You may report side effects to FDA at 1-800-FDA-1088. You may also report side effects to www.fda.gov/medwatch or Piramal Critical Care, Inc. at 1-800-414-1901 or FDA at 1-800-FDA-1088 or www.fda.gov/medwatch.

What are the ingredients in Edaravone injection?
Active ingredient: edaravone
Inactive ingredients: L-cysteine hydrochloride hydrate, sodium bisulfite, sodium chloride, phosphoric acid, and sodium hydroxide.

This Patient Information has been approved by the U.S. Food and Drug Administration.

Manufactured for:
Piramal Crtical Care, Inc.
Bethlehem, PA 18017, USA

Issued: 09/2023

PACKAGE LABEL.PRINCIPAL DISPLAY PANEL

Bag Label:

Edaravone Injection 30 mg/100 mL (0.3 mg/mL)

For Intravenous Infusion

NDC 66794-259-61

Pouch Label:

Edaravone Injection

30 mg/100 mL (0.3 mg/mL)

For Intravenous Infusion

NDC 66794-259-61

Carton Label:

Edaravone Injection 100 mL X 2 Bags

30 mg/100 mL (0.3 mg/mL)

NDC 66794-259-64

For Intravenous Infusion

Sterile Solution

Single-Dose-Discard unused portion

(Infuse each 30 mg/100 ml over period of 30 minutes)

Rx only